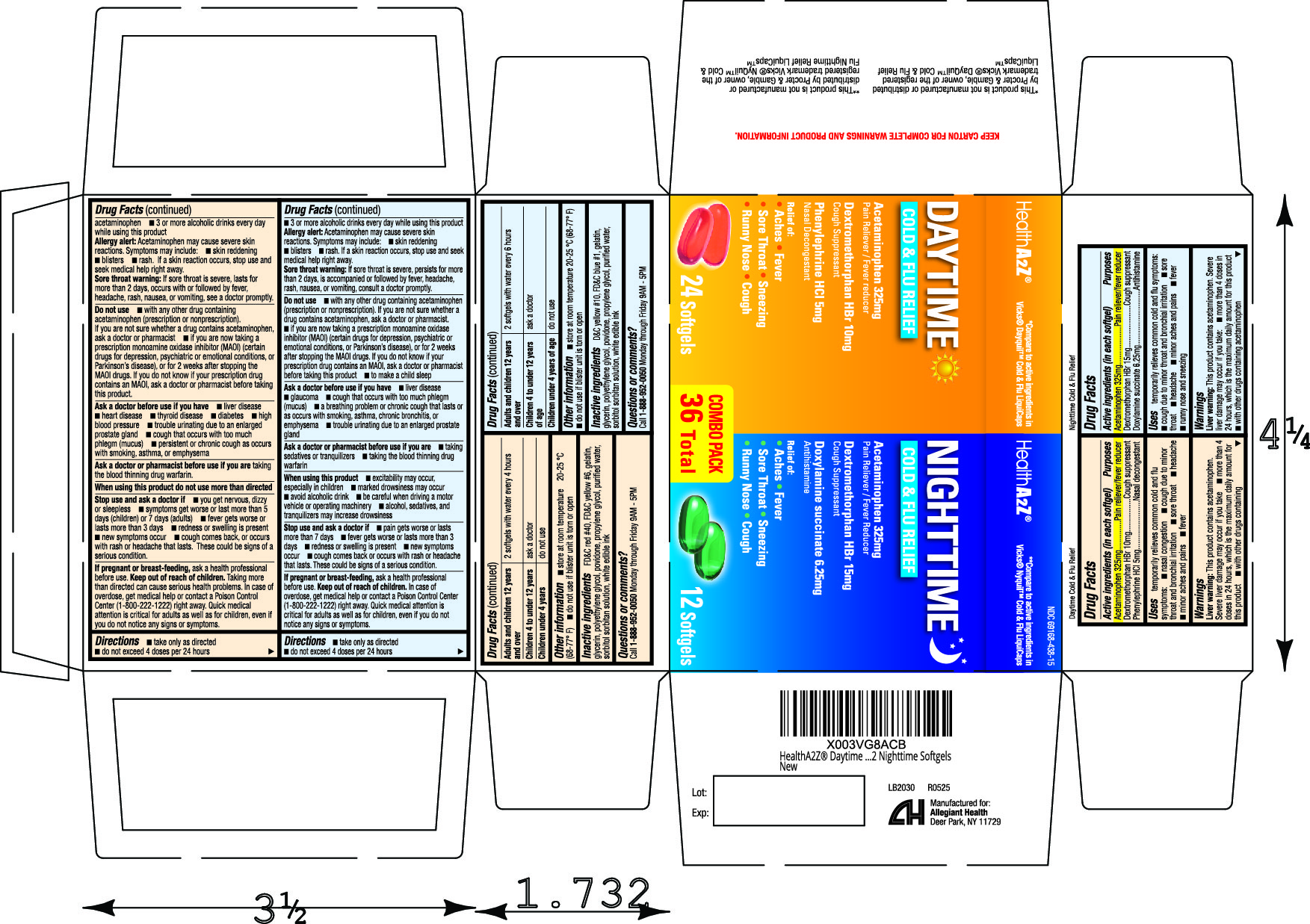 DRUG LABEL: Daytime Nighttime Cold and Flu Relief Combo Pack
NDC: 69168-438 | Form: KIT | Route: ORAL
Manufacturer: Allegiant Health
Category: otc | Type: HUMAN OTC DRUG LABEL
Date: 20220519

ACTIVE INGREDIENTS: ACETAMINOPHEN 325 mg/1 1; DEXTROMETHORPHAN HYDROBROMIDE 10 mg/1 1; PHENYLEPHRINE HYDROCHLORIDE 5 mg/1 1; ACETAMINOPHEN 325 mg/1 1; DEXTROMETHORPHAN HYDROBROMIDE 15 mg/1 1; DOXYLAMINE SUCCINATE 6.25 mg/1 1
INACTIVE INGREDIENTS: FD&C RED NO. 40; FD&C YELLOW NO. 6; GELATIN; GLYCERIN; POLYETHYLENE GLYCOL, UNSPECIFIED; POVIDONE; PROPYLENE GLYCOL; WATER; SORBITOL SOLUTION; D&C YELLOW NO. 10; FD&C BLUE NO. 1; GELATIN; GLYCERIN; POLYETHYLENE GLYCOL, UNSPECIFIED; POVIDONE; PROPYLENE GLYCOL; WATER; SORBITOL SOLUTION

438 - Daytime Nighttime Cold and Flu

Active ingredient(s)

DAYTIME ONLY

Acetaminophen 325mg
Dextromethorphan HBr 10mg
Phenylephrine HCl 5mg

NIGHTTIME ONLY

Acetaminophen 325mg
Dextromethorphan HBr 15mg
Doxylamine succinate 6.25mg

Purpose

DAYTIME ONLY

Pain reliever/fever reducer
Cough suppressant
Nasal decongestant

NIGHTTIME ONLY

Pain reliever/fever reducer
Cough suppressant
Antihistamine

Use(s)

DAYTIME ONLY

temporarily relieves common cold/flu symptoms: • nasal
congestion • cough due to minor throat & bronchial irritation • sore
throat • headache • minor aches & pains • fever

NIGHTTIME ONLY

temporarily relieves common cold/flu symptoms:
• cough due to minor throat & bronchial irritation • sore throat • headache
• minor aches & pains • fever • runny nose & sneezing

Warnings

DAYTIME AND NIGHTTIME

Liver warning: This product contains acetaminophen.
Severe liver damage may occur if you take:
• more than 4 doses in 24 hrs, which is the maximum daily amount for this product
• with other drugs containing acetaminophen
• 3 or more alcoholic drinks every day while using this product

Allergy Alert: Acetaminophen may cause severe skin reactions.
Symptoms may include: • skin reddening • blisters • rash
If a skin reaction occurs, stop use and seek medical help right away.

Sore throat warning: If sore throat is severe, persists for more than 2 days,
occurs with or is followed by fever, headache, rash, nausea, or vomiting,
consult a doctor promptly.

Do not use

DAYTIME ONLY

• with any other drug containing acetaminophen (prescription
or nonprescription). If you are not sure whether a drug contains
acetaminophen, ask a doctor or pharmacist.
• if you are now taking a prescription monoamine oxidase inhibitor (MAOI)
(certain drugs for depression, psychiatric or emotional conditions, or
Parkinson's disease), or for 2 weeks after stopping the MAOI drug.
If you do not know if your prescription drug contains an MAOI, ask a
doctor or pharmacist before taking this product.

NIGHTTIME ONLY

• with any other drug containing acetaminophen (prescription or
nonprescription). If you are not sure whether a drug contains acetaminophen,
ask a doctor or pharmacist.
• if you are now taking a prescription monoamine oxidase inhibitor (MAOI) (certain
drugs for depression, psychiatric or emotional conditions, or Parkinson's disease),
or for 2 weeks after stopping the MAOI drug. If you do not know if your prescription
drug contains an MAOI, ask a doctor or pharmacist before taking this product.
• to make a child sleep

Ask a doctor before use if you have

DAYTIME ONLY

• liver disease • heart disease • thyroid disease • diabetes • high blood pressure
• trouble urinating due to an enlarged prostate gland • cough that occurs
with too much phlegm (mucus) • persistent or chronic cough as occurs
with smoking, asthma, or emphysema

NIGHTTIME ONLY

• liver disease •glaucoma • cough that occurs with too much phlegm (mucus)
• a breathing problem or chronic cough that lasts or as occurs with smoking,
asthma, chronic bronchitis or emphysema
• trouble urinating due to enlarged prostate gland

Ask a doctor or pharmacist before use if

DAYTIME ONLY

taking the blood thinning drug warfarin.

NIGHTTIME ONLY

• taking sedatives or tranquilizers
• taking the blood thinning drug warfarin

When using this product

DAYTIME ONLY

do not use more than directed

NIGHTTIME ONLY

• do not use more than directed
• excitability may occur, especially in children
• marked drowsiness may occur • avoid alcoholic drinks
• be careful when driving a motor vehicle or operating machinery
• alcohol, sedatives & tranquilizers may increase drowsiness

Stop use and ask a doctor if

DAYTIME ONLY

• you get nervous, dizzy or sleepless
• symptoms get worse or last more than 5 days (children) or 7 days (adults)
• fever gets worse or lasts more than 3 days
• redness or swelling is present •new symptoms occur
• cough comes back, or occurs with rash or headache that lasts.
These could be signs of a serious condition.

NIGHTTIME ONLY

• pain or cough gets worse or lasts more than 7 days
• fever gets worse or lasts more than 3 days
• redness or swelling is present • new symptoms occur
• cough comes back or occurs with rash or headache that lasts.
These could be signs of a serious condition.

Pregnancy/Breastfeeding

ask a health professional before use.

Keep out of reach of children

In case of overdose, get medical help or contact a Poison Control Center
(1-800-222-1222) right away. Quick medical attention is critical
for adults as well as for children, even if you do not notice any signs or symptoms.

Directions

DAYTIME ONLY

- Take only as directed
- Do not exceed 4 doses in 24 hrs

adults and children 12 yrs & over: 2 softgels with water every 4 hrs

children 4 to under 12 yrs: ask a doctor

children under 4 yrs: do not use

NIGHTTIME ONLY

- Take only as directed
- Do not exceed 4 doses in 24 hrs

adults and children 12 yrs & over: 2 softgels with water every 6 hrs

children 4 to under 12 yrs: ask a doctor

children under 4 yrs: do not use

Other information

- store at room temperature 20-25 °C (68-77° F)
- do not use if blister unit is torn or open

Inactive ingredients

DAYTIME ONLY

FD&C red #40, FD&C yellow #6, gelatin, glycerin, polyethylene glycol, povidone, propylene
glycol, purified water, sorbitol sorbitan solution, white edible ink

NIGHTTIME ONLY

D&C yellow #10, FD&C blue #1, gelatin, glycerin, polyethylene glycol, povidone, propylene
glycol, purified water, sorbitol sorbitan solution, white edible ink

Questions

Questions or comments?
Call 1-888-952-0050 Monday through Friday 9AM - 5PM

Principal Display Panel

Daytime and Nighttime